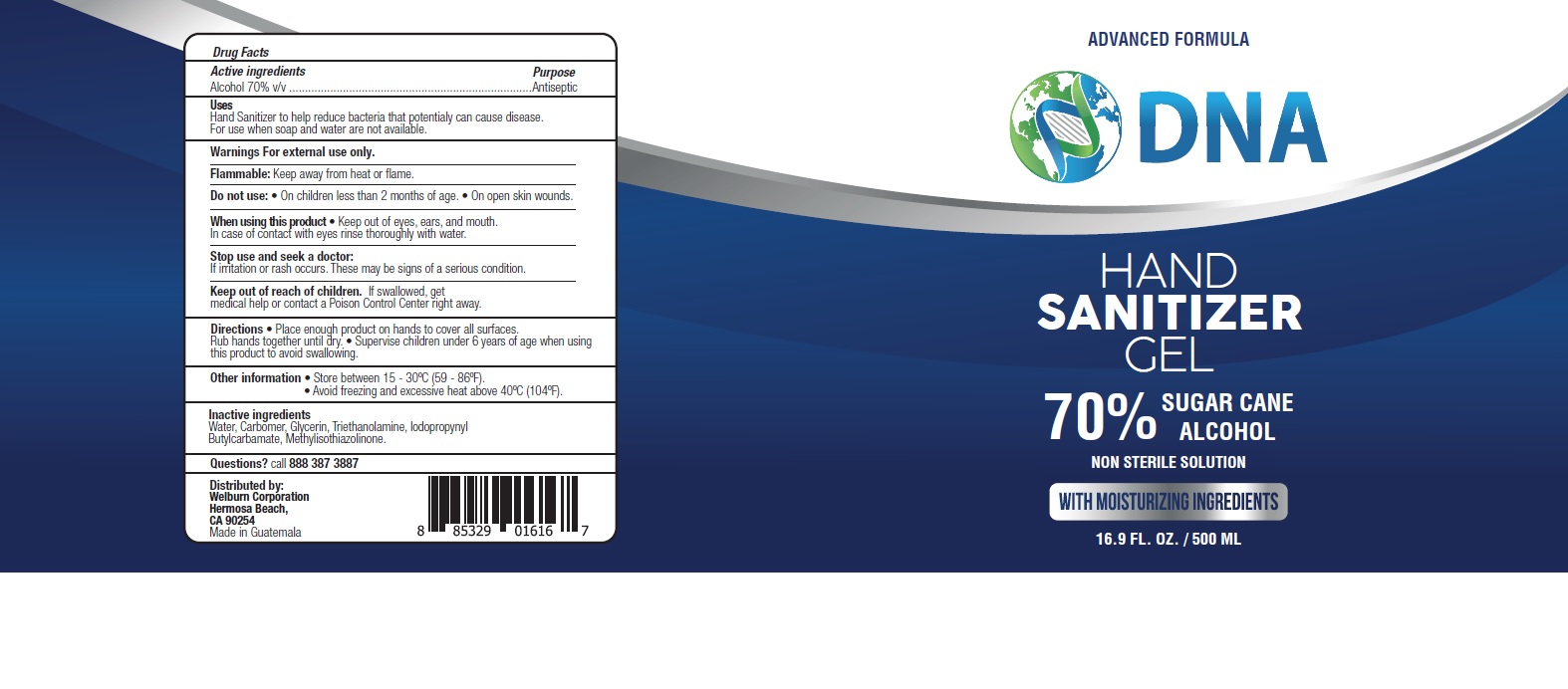 DRUG LABEL: DNA HAND SANITIZER
NDC: 77622-031 | Form: GEL
Manufacturer: Welburn Corporation
Category: otc | Type: HUMAN OTC DRUG LABEL
Date: 20201119

ACTIVE INGREDIENTS: ALCOHOL 70 mL/100 mL
INACTIVE INGREDIENTS: GLYCERIN; CARBOMER HOMOPOLYMER, UNSPECIFIED TYPE; METHYLISOTHIAZOLINONE; IODOPROPYNYL BUTYLCARBAMATE; TROLAMINE; WATER

DNA Hand Sanitizer

Active ingredients

Alcohol 70% v/v

Purpose

Antiseptic

Uses

Hand Sanitizer to help reduce bacteria that potentially can cause disease. For use when soap and water are not available.

Warnings

For external use only.

Flammable. Keep away from heat or flame.

Do not use

- On children less than 2 months of age.
- On open skin wounds.

When using this product

- Keep out of eyes, ears and mouth. In case of contact with eyes rinse thoroughly with water.

Stop use and seek a doctor

If irritation or rash occurs. These may be signs of a serious condition.

Keep out of reach of children.

If swallowed, get medical help or contact a Poison Control Center right away.

Directions

- Place enough product on hands to cover all surfaces. Rub hands together until dry.
- Supervise children under 6 years of age when using this product to avoid swallowing.

Other information

- Store between 15-30C (59-86F).
- Avoid freezing and excessive heat above 40C (104F).

Inactive ingredients

Water, Carbomer, Glycerin, Triethanolamine, Iodopropynyl Butylcarbamate, Methylisothiazolinone.

Questions?

call 888 387 3887

Company Information

Distributed by:

Welburn Corporation

Hermosa Beach, CA 90254

Made in Guatemala

Product Packaging - 500 ML

ADVANCED FORMULA

DNA

HAND

SANITIZER

GEL

70% SUGAR CANE ALCOHOL

NON STERILE SOLUTION

WITH MOISTURIZING INGREDIENTS

16.9 FL. OZ. / 500 ML